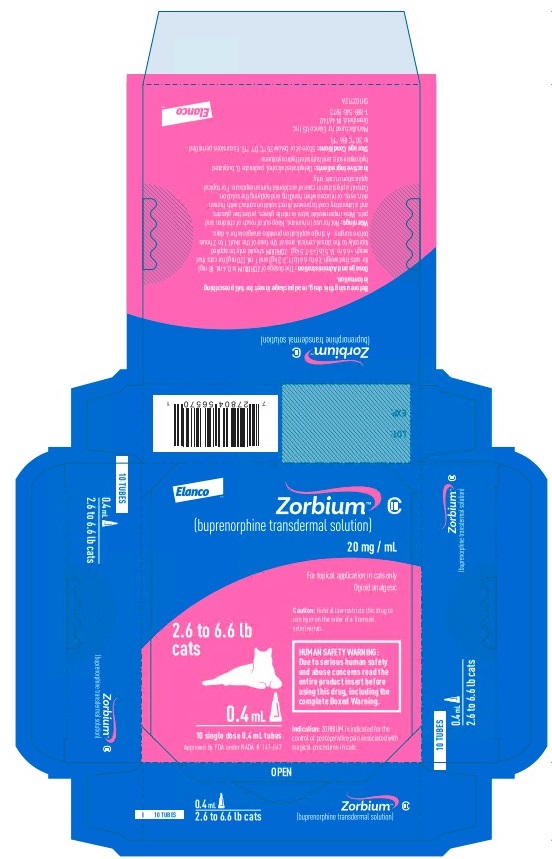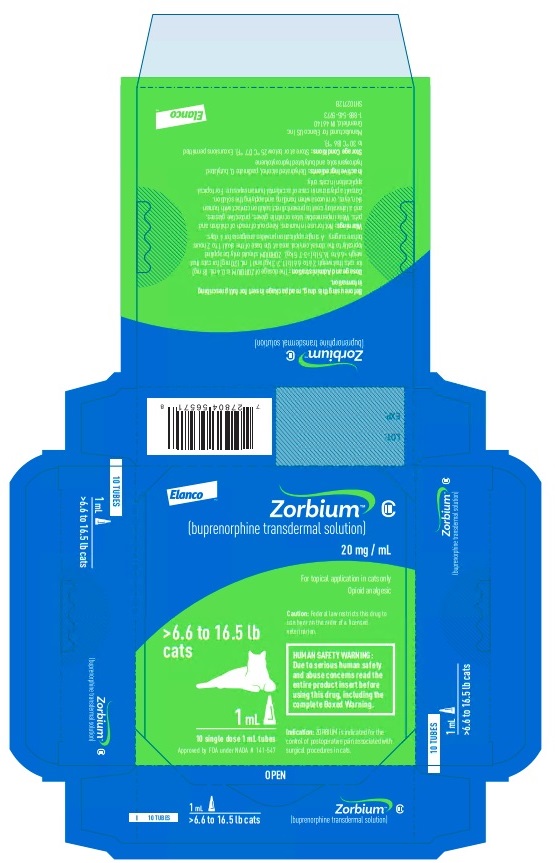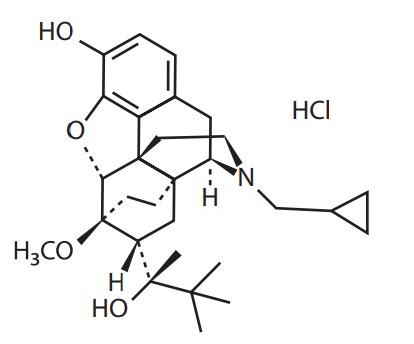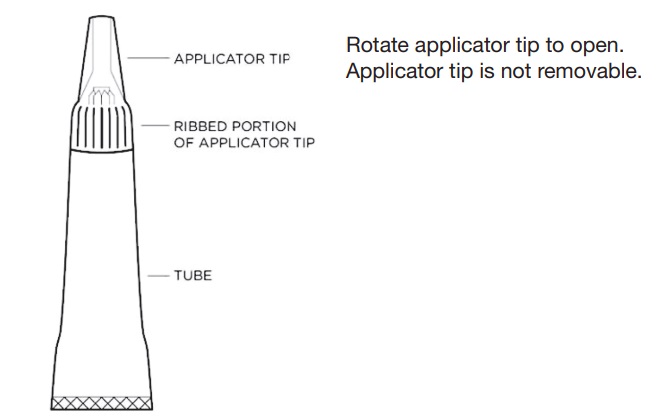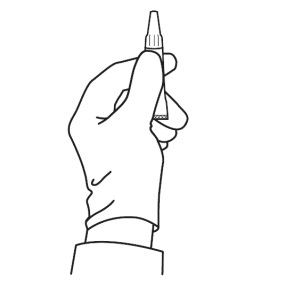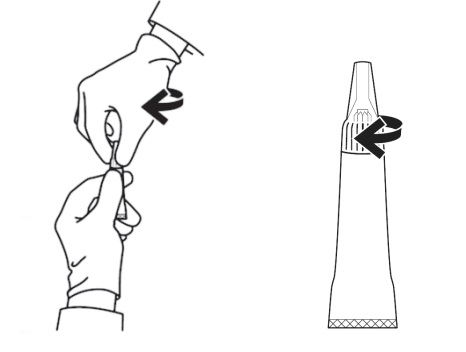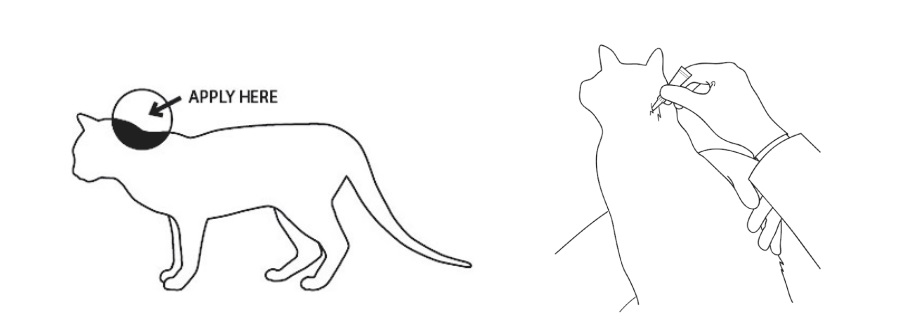 DRUG LABEL: Zorbium
NDC: 58198-0078 | Form: SOLUTION
Manufacturer: Elanco US Inc.
Category: animal | Type: PRESCRIPTION ANIMAL DRUG LABEL
Date: 20220425
DEA Schedule: CIII

ACTIVE INGREDIENTS: BUPRENORPHINE 20 mg/1 mL

ZorbiumTM
(buprenorphine transdermal solution)

For use in cats only

ZorbiumTM
(buprenorphine transdermal solution)
20 mg/mL

For topical application in cats
Opioid analgesic
CAUTION: Federal law restricts this drug to use by or on the order of a licensed veterinarian.

HUMAN SAFETY WARNING

Abuse Potential
ZORBIUM contains buprenorphine, an opioid that exposes humans to risks of misuse, abuse, and addiction, which can lead to overdose and death. Use of buprenorphine may lead to physical dependence. The risk of abuse by humans should be considered when storing, administering, and disposing of ZORBIUM. Persons at increased risk for opioid abuse include those with a personal or family history of substance abuse (including drugs or alcohol) or mental illness (e.g. depression).

Life-Threatening Respiratory Depression
Serious, life-threatening, or fatal respiratory depression may occur with accidental exposure to or with misuse or abuse of ZORBIUM. Monitor for respiratory depression if human exposure to buprenorphine occurs. Misuse or abuse of buprenorphine by swallowing, snorting, or injecting poses a significant risk of overdose and death.

Accidental Exposure
Because of the potential for adverse reactions associated with accidental exposure, ZORBIUM should only be administered by veterinarians or veterinary technicians who are trained in the handling of potent opioids. Accidental exposure to even one tube of ZORBIUM, especially in children, can result in a fatal overdose of buprenorphine.

Risks From Concurrent Misuse or Abuse with Benzodiazepines or Other CNS Depressants Concurrent misuse or abuse of opioids with benzodiazepines or other central nervous system (CNS) depressants, including alcohol, may result in profound sedation, respiratory depression, coma, and death.

See Human Safety Warnings for detailed information.

DESCRIPTION:

ZORBIUM is a volatile liquid transdermal solution intended for topical application that provides continuous, systemic delivery of the opioid analgesic, buprenorphine. Buprenorphine belongs to the opioid class of drugs and is a narcotic under the Controlled Substances Act due to its chemical derivation from thebaine. Once ZORBIUM is applied to the skin, rapid drying results in dermal absorption and sequestration of buprenorphine into the stratum corneum. Each mL of ZORBIUM contains 20 mg buprenorphine (administered as 21.56 mg of buprenorphine hydrochloride). The inactive ingredients are dehydrated alcohol, padimate O, butylated hydroxyanisole, and butylated hydroxytoluene.
Buprenorphine hydrochloride has an empirical formula of C29H41NO4 •HCl and a molecular weight of 504.10.
The chemical structure of buprenorphine HCl is:

INDICATION:

ZORBIUM is indicated for the control of postoperative pain associated with surgical procedures in cats.

DOSAGE AND ADMINISTRATION:

This product should only be administered by veterinary personnel.

ZORBIUM is for administration only once for the surgical procedure. ZORBIUM should be applied 1 to 2 hours before surgery. A single application provides analgesia for 4 days. ZORBIUM should only be applied topically to the dorsal cervical area at the base of the skull. Do not apply if dorsal cervical skin is diseased or injured. The dosage of ZORBIUM is 1.2 – 3.1 mg/lb (2.7 – 6.7 mg/kg) administered topically as the entire tube contents according to the following dosing table:

Pounds of Body Weight | Kilograms of Body Weight | Dose of ZORBIUM
2.6 to 6.6 | 1.2 to 3 | 0.4 mL (8 mg) pink tube
>6.6 to 16.5 | >3 to 7.5 | 1 mL (20 mg) green tube

Dose Application
Wear impermeable latex or nitrile gloves, protective glasses, and a laboratory coat to prevent direct solution contact with human skin, eyes, or mucosa when handling and applying the solution. Do not dispense ZORBIUM for administration at home by the pet owner (see HUMAN SAFETY WARNINGS).

Figure 1 - Diagram of tube components.

Figure 2 – Proper grasp of the applicator tube: To prepare to open the tube for application, the tube must be held in an upright position to avoid spilling contents. Grasp the tube just beneath the ribbed portion of the tip.

Figure 3 – Opening the applicator tube: Keeping the tube upright, grasp the ribbed portion of the tip, and turn the applicator tip in either direction at least 180° to open the tube. The applicator tip is designed to stay on the tube and should not be removed. The tube is ready for application when a breaking of the seal is felt.

Figure 4 – Solution application: Fur should not be clipped. Do not apply to injured or diseased skin. Gently hold the cat both before and after application to prevent the cat from shaking or rubbing.

Part the fur and apply the tip of the tube directly onto the skin at the base of the head. Squeeze the tube 2 – 3 times to empty the contents without moving the tube or the tip. Lift the tube directly away from the skin, avoiding contact of the tip with the cat’s fur.

CONTRAINDICATIONS:

ZORBIUM is contraindicated in cats with known hypersensitivity to buprenorphine hydrochloride, any of the inactive ingredients of ZORBIUM, or known intolerance to opioids.

WARNINGS:

HUMAN SAFETY WARNINGS:
Not for use in humans. Keep this and all medications out of reach of children and pets.

Human User Safety While Handling ZORBIUM in the Hospital:
Protective Covering: Do not come into direct contact with ZORBIUM. Wear impermeable latex or nitrile gloves, protective glasses, and a laboratory coat when applying ZORBIUM.

Mucous Membrane or Eye Contact During Application:
Direct contact of ZORBIUM with the eyes, oral, or other mucous membranes could result in absorption of buprenorphine and the potential for adverse reactions. If accidental eye, oral, or other mucous membrane contact is made during application, flush the area with water and contact a physician immediately. If wearing contact lenses, flush the eye first and then remove the contact lens.

Skin Contact During Application:
Following application to the cat, allow a minimum drying time of 30 minutes before direct contact with the application site. If human skin is accidentally exposed to ZORBIUM, wash the exposed area immediately with soap and water and contact a physician. Accidental exposure could result in absorption of buprenorphine and the potential for adverse reactions.

Drug Abuse, Addiction, and Diversion of Opioids:
Controlled Substance:
ZORBIUM contains buprenorphine, a Schedule III controlled substance with an abuse potential similar to other Schedule III opioids.

Abuse:
ZORBIUM contains buprenorphine, an opioid substance, that can be abused and is subject to misuse, abuse, and addiction, which may lead to overdose and death. This risk is increased with concurrent use of alcohol and other central nervous system depressants, including other opioids and benzodiazepines.

ZORBIUM should be handled appropriately to minimize the risk of diversion, including restriction of access, the use of accounting procedures, and proper disposal methods, as appropriate to the clinical setting and as required by law.

Prescription drug abuse is the intentional, non-therapeutic use of a prescription drug, even once, for its rewarding psychological or physiological effects. Buprenorphine has been diverted for non-medical use into illicit channels of distribution. All people handling opioids require careful monitoring for signs of abuse.

Storage and Disposal:
ZORBIUM is a Schedule III opioid. Store in a locked cabinet according to federal and state controlled substance requirements/guidelines. Any unused or expired tubes must be destroyed by a reverse distributor; for further information, contact your local DEA field office or call Elanco US Inc. at 1-888-545-5973.

Information for Physician:
ZORBIUM transdermal solution contains a mu opioid partial agonist (20 mg buprenorphine/mL). In the case of an emergency, provide the physician with this package insert. Naloxone may not be effective in reversing respiratory depression produced by buprenorphine. The onset of naloxone effect may be delayed by 30 minutes or more. Doxapram hydrochloride has also been used as a respiratory stimulant.

ANIMAL SAFETY WARNINGS:
For topical use in cats only. This product should only be administered by veterinary personnel.
Do not apply ZORBIUM if the application site at the dorsal cervical area has diseased or injured skin.
Do not apply ZORBIUM to anatomic areas other than the dorsal cervical area because absorption characteristics may be different.

PRECAUTIONS:

Following anesthesia and opioid analgesia, body temperature should be monitored postoperatively for immediate hypothermia and subsequent hyperthermia. Hyperthermia can occur and persist after the hypothermic effects of anesthesia have resolved.

The safe use of ZORBIUM has not been evaluated in debilitated cats or cats with renal, hepatic, cardiac, or respiratory disease.

The safe use of ZORBIUM has not been evaluated in cats that are pregnant, lactating, or intended for breeding.

The safe use of ZORBIUM has not been evaluated in cats younger than four months old.

The safe use of ZORBIUM has not been evaluated in cats weighing less than 2.6 pounds or more than 16.5 pounds.

ADVERSE REACTIONS:

In a randomized, multi-centered, double-masked, field study, ZORBIUM™ (buprenorphine transdermal solution) (N=113) or vehicle control (N=109) was administered to cats prior to elective surgical reproductive sterilization (castration/ovariohysterectomy) in conjunction with forelimb onychectomy. Cats enrolled in the study were 4 months to 5 years of age and weighed 1.1 to 5.7 kg (2.5 to 12.5 lb). Clinical observations and physiological parameters were monitored prior to, during, and after surgery for 96 hours after sternal recumbency.
Supplemental heat and fluids were allowed. There were no deaths during the study and no cats received an opioid reversal agent. Three ZORBIUM and 2 vehicle control cats were removed due to hyperthermia suspected to be treatment related. One ZORBIUM cat was removed due to fractious behavior 30 minutes following surgery. Adverse reactions were defined as any single excursion outside the normal range, as defined: 100.5 – 102.5 ˚F body temperature; 60 – 120 mmHg mean arterial pressure; 88 – 180 beats per minute for heart rate; 24 – 44 breaths per minute for respiratory rate. A summary of adverse reactions during anesthesia (from anesthetic induction through recovery defined as sternal recumbency) is provided in Table 1.

Table 1. Adverse Reactions During Anesthesia:
Adverse Reaction* | ZORBIUM (N=113) | Vehicle Control (N=109)
Hypothermia | 37 (32.7%) | 29 (26.6%)
Hypotension | 31 (27.4%) | 28 (25.7%)
Hypertension | 27 (23.9%) | 18 (16.5%)
Tachycardia | 14 (12.4%) | 14 (12.8%)
Sedation | 12 (10.6%) | 7 (6.4%)
Oxygen saturation ≤ 90% | 6 (5.3%) | 2 (1.8%)
Bradycardia | 4 (3.5%) | 2 (1.8%)
Hyperthermia | 3 (2.7%) | 4 (3.7%)
*Physiological adverse reactions were defined as any single excursion outside the normal range at any 10 minute interval during the entire duration of anesthesia.

After recovery, cats were observed in the hospital and underwent physiological assessments that included indirect mean arterial blood pressure, heart rate, respiratory rate, body temperature, lung auscultation, heart auscultation, and assessments of urination, defecation, and appetite. A summary of adverse reactions after anesthetic recovery (sternal recumbency) in all cats is reported in Table 2.

Table 2. Adverse Reactions After Anesthetic Recovery:
Adverse Reaction* | ZORBIUM (N=113) | Vehicle Control (N=109)
Hypothermia | 107 (94.7%) | 105 (96.3%)
Hyperthermia | 84 (74.3%) | 62 (56.9%)
Sedation | 64 (56.6%) | 48 (44.0%)
Tachypnea | 56 (49.6%) | 70 (64.2%)
Hypotension | 50 (44.2%) | 51 (46.8%)
Hypertension | 42 (37.2%) | 34 (31.2%)
Bradycardia | 34 (30.1%) | 45 (41.3%)
Tachycardia | 32 (28.3%) | 39 (35.8%)
Anorexia | 25 (22.1%) | 32 (29.4%)
Dysphoria | 20 (17.7%) | 29 (26.6%)
Diarrhea | 11 (9.7%) | 11 (10.1%)
Bradypnea | 11 (9.7%) | 7 (6.4%)
Leukocytosis | 6 (5.3%) | 4 (3.7%)
Hyperactivity | 2 (1.8%) | 9 (8.3%)
*Physiological adverse reactions were defined as any single excursion outside the normal range following anesthetic recovery (sternal recumbency) through 4 days postoperatively.

Hyperthermia was the only adverse event observed in more than 10% of cats in the ZORBIUM group after the day of surgery (24 – 96 hours). The percentage of cats in the ZORBIUM group with hyperthermia decreased over time from 66.4% on Day 0 to 28.3% on Day 1, and to 6.2% by Day 4. A summary of adverse reactions (from anesthetic recovery through 96 hours after recovery) in cats in the ZORBIUM group by study day is reported in Table 3.

Table 3. Adverse Reactions in ZORBIUM Cats (N=113) by Day:
Adverse Reaction* | Day 0 | Day 1 | Day 2 | Day 3 | Day 4
Hypothermia | 106 (93.8%) | 2 (1.8%) | 2 (1.8%) | 2 (1.8%) | 2 (1.8%)
Hyperthermia | 75 (66.4%) | 32 (28.3%) | 18 (15.9%) | 14 (12.4%) | 7 (6.2%)
Sedation | 64 (56.6%) | 0 (0.0%) | 0 (0.0%) | 0 (0.0%) | 0 (0.0%)
Tachypnea | 51 (45.1%) | 5 (4.4%) | 2 (1.8%) | 3 (2.7%) | 4 (3.5%)
Hypotension | 42 (37.2%) | 2 (1.8%) | 1 (0.9%) | 4 (3.5%) | 2 (1.8%)
Hypertension | 28 (24.8%) | 2 (1.8%) | 1 (0.9%) | 1 (0.9%) | 1 (0.9%)
Anorexia | 25 (22.1%) | 3 (2.7%) | 1 (0.9%) | 0 (0.0%) | 0 (0.0%)
Bradycardia | 24 (21.2%) | 3 (2.7%) | 2 (1.8%) | 3 (2.7%) | 5 (4.4%)
Tachycardia | 24 (21.2%) | 4 (3.5%) | 0 (0.0%) | 1 (0.9%) | 1 (0.9%)
Dysphoria | 20 (17.7%) | 0 (0.0%) | 0 (0.0%) | 0 (0.0%) | 0 (0.0%)
Bradypnea | 8 (7.1%) | 2 (1.8%) | 0 (0.0%) | 0 (0.0%) | 1 (0.9%)
Hyperactivity | 1 (0.9%) | 0 (0.0%) | 0 (0.0%) | 0 (0.0%) | 1 (0.9%)
*Physiological adverse reactions were defined as any single excursion outside the normal range following anesthetic recovery (sternal recumbency) through 96 hours postoperatively.

CONTACT INFORMATION:

To report suspected adverse events, for technical assistance, or to obtain a copy of the Safety Data Sheet (SDS), contact Elanco US Inc. at 1-888-545-5973.

For additional information about reporting adverse drug experience for animal drugs, contact FDA at 1-888-FDA-VETS or http://www.fda.gov/reportanimalae.

CLINICAL PHARMACOLOGY:

Mechanism of Action: Buprenorphine exerts its analgesic effect via high affinity binding to various subclasses of opiate receptors, particularly mu, in the central nervous system. Buprenorphine analgesic and adverse reactions are mediated by mu opioid receptor agonism. Due to its partial agonist activity, buprenorphine exhibits a ceiling effect to its actions and thus has a greater therapeutic index compared to full mu opioid receptor agonists such as morphine. Buprenorphine binds tightly to and disassociates slowly from the opioid receptor. Therefore, the pharmacological effects of buprenorphine are not directly related to plasma concentrations.

Pharmacokinetics: Following application of ZORBIUM, solvent evaporation coupled with the permeation enhancer action results in rapid absorption and sequestration of the buprenorphine into the skin. ZORBIUM provides analgesia within 1 – 2 hours following administration and continually releases buprenorphine from the skin into the systemic circulation over a period of days. The mean (range) time to reach peak concentration (tmax) was 7.33 (1 – 24) hours. Due to buprenorphine elimination being faster than absorption from the skin, ZORBIUM exhibits flip-flop pharmacokinetics where the absorption determines its terminal half-life (mean 64.9 hours [range 39.1 – 85.7 hours]). The estimated absolute bioavailability (F) of transdermal administration was in the order of 16% [90% confidence interval (CI) =11.8% – 21.7%].

Buprenorphine is extensively metabolized by the liver in humans, the primary route being N-dealkylation to norbuprenorphine by cytochrome P450 enzymes. Both buprenorphine and norbuprenorphine form inactive glucuronide conjugates and are excreted by the bile into the gastrointestinal tract. The cat is devoid of uridine diphosphate glucuronosyltransferase enzymes (UGT1A6 and UGT1A9) responsible for conjugation and therefore conjugated metabolites may be absent. Norbuprenorphine is considered an active metabolite of buprenorphine, though it has one-fiftieth the analgesic activity of buprenorphine in rats. Buprenorphine extensively binds (95 – 98%) to plasma proteins.

EFFECTIVENESS:

The effectiveness of ZORBIUM was demonstrated in cats that underwent elective reproductive sterilization in conjunction with forelimb onychectomy surgery in a randomized, multi-centered, double-masked, vehicle-controlled, field study across 12 investigative sites. Enrolled cats were between 4 months to 5 years of age and weighed 2.5 to 12.5 pounds (1.1 – 5.7 kg).

Cats in the ZORBIUM group received a single dose of 8 mg or 20 mg of buprenorphine according to body weight (see DOSAGE AND ADMINISTRATION). Cats in the vehicle control group received a transdermal solution of 50 mg/mL padimate O in ethanol. The dose was administered topically onto the dorsal cervical skin 1 – 2 hours prior to anesthetic induction for surgery. For intraoperative analgesia, all cats in the study received a single intramuscular injection of an alpha2-agonist 30 minutes prior to anesthetic induction, and a 4-point metacarpal ring block with lidocaine after induction. The adequacy of pain control was scored through 96 hours after surgery. If pain control was considered inadequate at any time following treatment, rescue analgesia was provided immediately. Treatment success was defined as a cat that did not require rescue analgesia, need opioid reversal, or experience an adverse event suspected to be related to treatment through the entire 96-hour post-recovery period. A cat was considered a treatment failure if it had inadequate pain control, required opioid reversal, or experienced an adverse event suspected to be related to treatment.

A total of 19 ZORBIUM and 63 vehicle control cats were removed from the study due to inadequate pain control. Most of these failures occurred on the day of surgery in both groups; however, there were 4 ZORBIUM group cats and 5 vehicle control cats removed due to inadequate pain control between 1 and 3 days after surgery.

Effectiveness was evaluated in 219 cats (112 in the ZORBIUM group and 107 cats in the vehicle control group), and field safety was evaluated in 222 cats (113 cats in the ZORBIUM group and 109 cats in the vehicle control group). Of the 112 cats in the ZORBIUM group, 89 were treatment successes; of the 107 vehicle control cats, 42 were treatment successes. Comparison of the ZORBIUM group and the vehicle control group demonstrated a statistically significant difference in the treatment success rates (p = 0.0003).

Hypothermia was common in both groups during surgery. The overall mean postoperative body temperature was higher in the ZORBIUM group than in the vehicle control group. Mean postoperative body temperatures in the ZORBIUM group were above the normal range at 4 and 8 hours postoperatively (mean±SD of 102.7°±1.2 °F and 102.6°±1.0 °F, respectively [normal range: 100.5 – 102.5 °F]). Mean indirect arterial blood pressure (MAP) was similar between the 2 treatment groups over time. Urination, defecation, appetite, and daily body weights after surgery were not affected by ZORBIUM administration. Fifteen cats in the ZORBIUM group had an increased fibrinogen at discharge, compared to 2 cats in the vehicle control group.

Fluid administration (intravenous and subcutaneous) and supplemental heat support after surgery were the most common concurrent treatments and were used similarly in both groups.

TARGET ANIMAL SAFETY:

Twelve Day Target Animal Safety Study: In a 12-day laboratory study, ZORBIUM was administered to 32 healthy four-month-old domestic cats (8 cats per group) at 0 mg/kg (vehicle control), 6.7 mg/kg (1X), 13.3 mg/kg (2X), and 20 mg/kg (3X) as a topical application to the dorsal cervical area every 4 days for a total of 3 doses. Dose-independent euphoria, mild dysphoria, and mydriasis were observed after ZORBIUM administration. Maximum scores (for euphoria, dysphoria, and mydriasis) in the ZORBIUM groups reached 3 (mildly dysphoric) between 1 – 2 hours after the first dose. On the other 2 dosing days (Days 4 and 8), maximum scores were 2 (euphoric). Euphoria in some cats persisted from 36 to 72 hours.

On dosing day 1, mydriasis was observed in approximately half the cats administered ZORBIUM by 24 hours after dosing (peaked in all ZORBIUM groups at 8 hours) and was not observed between 48 – 93 hours. After the day 8 dose (third dose), it was rarely observed (1 cat in 1X group; 2 cats in 3X at 48 hours; 1 cat in 2X at 72 hours).

Cats administered ZORBIUM had higher body temperatures compared to the vehicle control group throughout the study. Following the initial dose, the mean temperatures in cats administered ZORBIUM increased above normal and were up to 1.8 ºF greater than the vehicle control group. Increased body temperature primarily occurred during the first 8 hours after the initial dose and was observed in the majority of cats administered ZORBIUM. Elevated temperatures ranged from 102.6 °F to 104.5 °F. The highest temperatures occurred at 2 hours after the first dose, gradually decreasing by 24 hours. By 3 days after dose administration, body temperatures in cats administered ZORBIUM had returned to levels observed in the vehicle control group. After the second and third doses (days 4 and 8), mean temperatures in all ZORBIUM groups were again higher than in the vehicle control group, but not higher than the normal reference range.

Constipation was recorded for 20 cats (1 vehicle control; 3 in 1X; 4 in 2X; 6 in 3X groups) after the first dose. The constipation was mild and transient. Three cats (2 in the 1X group and 1 in the 3X group) were administered a laxative. ZORBIUM had no clinically significant effects on heart rate or respiratory rate. There were no clinically relevant changes to serum chemistry, hematology, or urinalysis outcomes. Histopathology evaluations revealed mild inflammation of skin at the application site.

Seven Day Target Animal Safety Study: In a 7-day laboratory study, ZORBIUM was administered once topically to the dorsal cervical area of 24 healthy adult domestic cats (6 cats/group) at 0 mg/kg (0X; vehicle control), 3.3 (0.5X), 10 (1.5X), or 30 mg/kg (4.5X the maximal dose of 6.7 mg/kg). Cats were observed for 7 days after the single dose. Clinical results were similar to the 12-day margin of safety study, even at the higher dose of 30 mg/kg, except for transient increases in heart rate in the ZORBIUM groups compared to the vehicle control group. Mean heart rates in ZORBIUM groups were higher than in the vehicle control group from 2 hours through approximately 48 hours after dose administration. Tachycardia (>240 beats per minute) occurred in two cats in the 0.5X group and two cats in the 4.5X group for at least one timepoint after dose administration. The highest heart rate was 260 (in the 0.5X group) and no dose relationship was evident. Dose-independent euphoria, mild dysphoria, and mydriasis were noted in the ZORBIUM groups. Mild constipation and/or abdominal distension were observed with ZORBIUM administration. Transient increases in plasma chloride and sodium concentrations in the ZORBIUM groups compared to vehicle control group indicated mild dehydration.

Cardiovascular Safety Study: In a 12-day cardiovascular laboratory safety study, ZORBIUM was administered to 8 healthy adult cats (4 cats per group) at 0 mg/kg (vehicle control) and 6.7 mg/kg (1X) as a topical application to the dorsal cervical region every 4 days for a total of 3 doses. Continuous, direct physiological monitoring (telemetry) was conducted from 2 hours prior to the first dose through 4 days following the third (final) dose. Body temperature increases averaged <0.4 oF in ZORBIUM group cats over vehicle control cats. In the vehicle control group, 102.6 °F was the maximum temperature, observed at 93 hours after the first dose. In the ZORBIUM group, 103.4 °F was the maximum temperature, observed at 20 hours after the first dose. Heart rate (HR) increased an average of 15.2 beats/minute in the ZORBIUM group cats compared to vehicle control cats. The maximum heart rate in the ZORBIUM group reached 231 beats/minute. In the vehicle control group, the maximum heart rate was 219 beats/minute. Blood pressure (arterial systolic, diastolic, and mean) in the ZORBIUM group cats was not significantly different from the vehicle control cats. There were no clinically significant effects of ZORBIUM on qualitative electrocardiogram results.

STORAGE INFORMATION:

Store at or below 25 °C (77 °F). Excursions permitted to 30 °C (86 °F).

HOW SUPPLIED:

ZORBIUM is available in applicator tubes that deliver a dose volume of 0.4 mL or 1 mL (20 mg/mL buprenorphine) in multi-packs of 10 tubes.

Approved by FDA under NADA # 141-547

Manufactured for:
Elanco US Inc.
Greenfield, IN 46140 USA

ZORBIUM, Elanco and the diagonal bar logo are trademarks of Elanco or its affiliates.
© 2021 Elanco or its affiliates

Rev. Date 02/2022

PA102712X
ElancoTM

PACKAGE/LABEL PRINCIPAL DISPLAY PANEL

ElancoTM

ZorbiumTM
(buprenorphine transdermal solution)

20 mg/mL

For topical application in cats only

Opioid analgesic

2.6 to 6.6 lb
cats

0.4 mL

10 single dose 0.4 mL tubes

Approved by FDA under NADA # 141-547

Caution: Federal law restricts this drug to
use by or on the order of a licensed
veterinarian.

HUMAN SAFETY WARNING:
Due to serious human safety
and abuse concerns read the
entire product insert before
using this drug, including the
complete Boxed Warning.

Indication: ZORBIUM is indicated for the
control of postoperative pain associated with
surgical procedures in cats.

PACKAGE/LABEL PRINCIPAL DISPLAY PANEL

ElancoTM

ZorbiumTM
(buprenorphine transdermal solution)

20 mg/mL

For topical application in cats only

Opioid analgesic

>6.6 to 16.5 lb
cats

1 mL

10 single dose 1 mL tubes

Approved by FDA under NADA # 141-547

Caution: Federal law restricts this drug to
use by or on the order of a licensed
veterinarian.

HUMAN SAFETY WARNING:
Due to serious human safety
and abuse concerns read the
entire product insert before
using this drug, including the
complete Boxed Warning.

Indication: ZORBIUM is indicated for the
control of postoperative pain associated with
surgical procedures in cats.